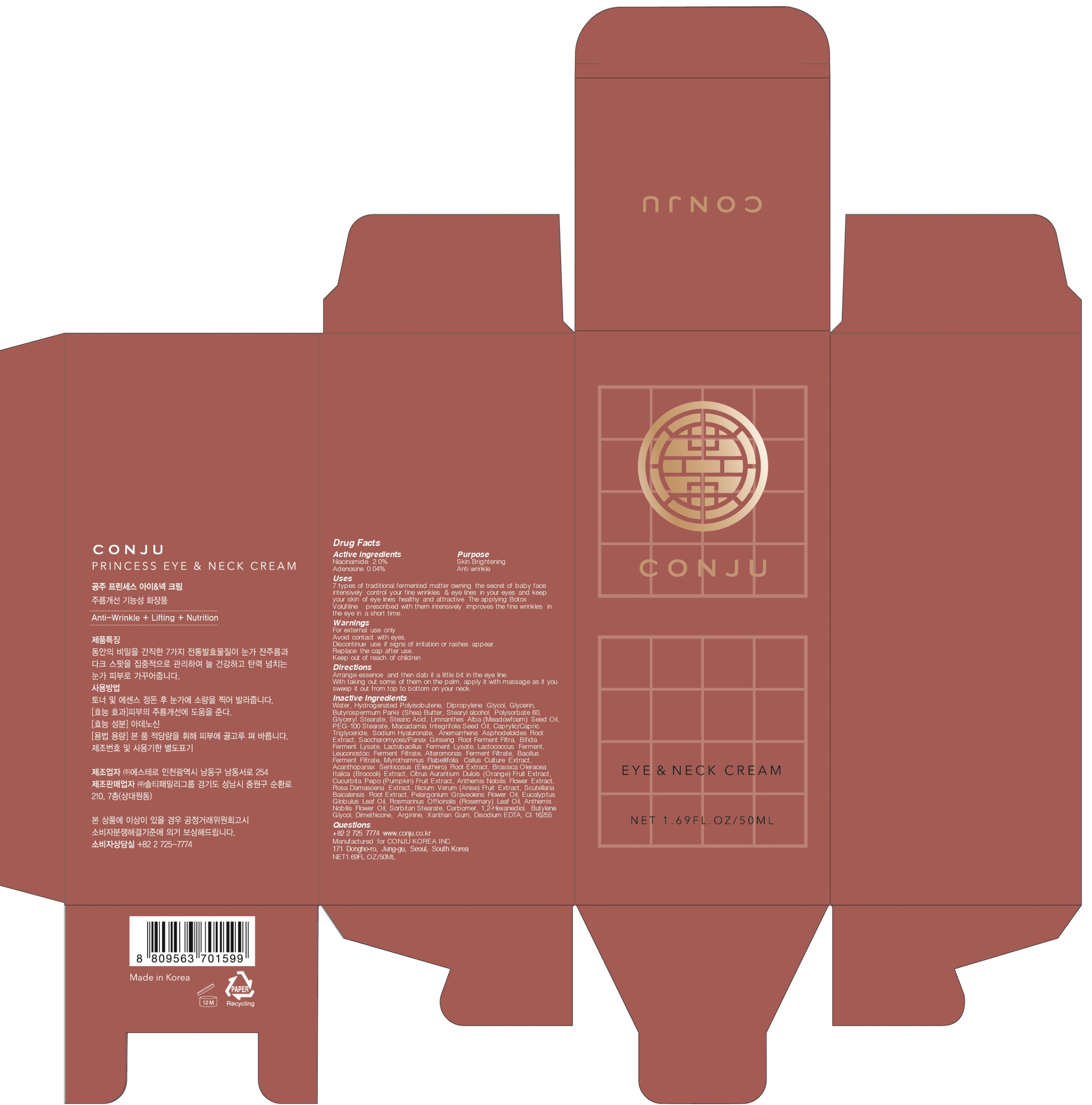 DRUG LABEL: CONGJU PRINCESS EYE AND NECK
NDC: 72950-030 | Form: CREAM
Manufacturer: Conju Korea Inc.
Category: otc | Type: HUMAN OTC DRUG LABEL
Date: 20190318

ACTIVE INGREDIENTS: Niacinamide 1.0 g/50 mL; Adenosine 0.02 g/50 mL
INACTIVE INGREDIENTS: Water; Dipropylene Glycol

ACTIVE INGREDIENT

Active ingredient: Niacinamide 2.0%, Adenosine 0.04%

INACTIVE INGREDIENT

Inactive ingredients:

Water, Hydrogenated Polyisobutene, Dipropylene Glycol, Glycerin, Butyrospermum Parkii (Shea) Butter, Stearyl alcohol, Polysorbate 60, Glyceryl Stearate, Stearic Acid, Limnanthes Alba (Meadowfoam) Seed Oil, PEG-100 Stearate, Macadamia Integrifolia Seed Oil, Caprylic/Capric Triglyceride, Sodium Hyaluronate, Anemarrhena Asphodeloides Root Extract, Saccharomyces/Panax Ginseng Root Ferment Filtra, Bifida Ferment Lysate, Lactobacillus Ferment Lysate, Lactococcus Ferment, Leuconostoc Ferment Filtrate, Alteromonas Ferment Filtrate, Bacillus Ferment Filtrate, Myrothamnus Flabellifolia Callus Culture Extract, Acanthopanax Senticosus (Eleuthero) Root Extract, Brassica Oleracea Italica (Broccoli) Extract, Citrus Aurantium Dulcis (Orange) Fruit Extract, Cucurbita Pepo (Pumpkin) Fruit Extract, Anthemis Nobilis Flower Extract, Rosa Damascena Extract, Illicium Verum (Anise) Fruit Extract, Scutellaria Baicalensis Root Extract, Pelargonium Graveolens Flower Oil, Eucalyptus Globulus Leaf Oil, Rosmarinus Officinalis (Rosemary) Leaf Oil, Anthemis Nobilis Flower Oil, Sorbitan Stearate, Carbomer, 1,2-Hexanediol, Butylene Glycol, Dimethicone, Arginine, Xanthan Gum, Disodium EDTA, CI 16255

PURPOSE

Purpose: Skin Brightening, Anti wrinkle

WARNINGS

For external use only
Avoid contact with eyes.
Discontinue use if signs of irritation or rashes appear.
Replace the cap after use.
Keep out of reach of children

KEEP OUT OF REACH OF CHILDREN

Uses

7 types of traditional fermented matter owning the secret of baby face intensively control your fine wrinkles & eye lines in your eyes and keep your skin of eye lines healthy and attractive. The applying Botox Volufiline prescribed with them intensively improves the fine wrinkles in the eye in a short time.

Directions

Arrange essence and then dab it a little bit in the eye line.
With taking out some of them on the palm, apply it with massage as if you sweep it out from top to bottom on your neck.